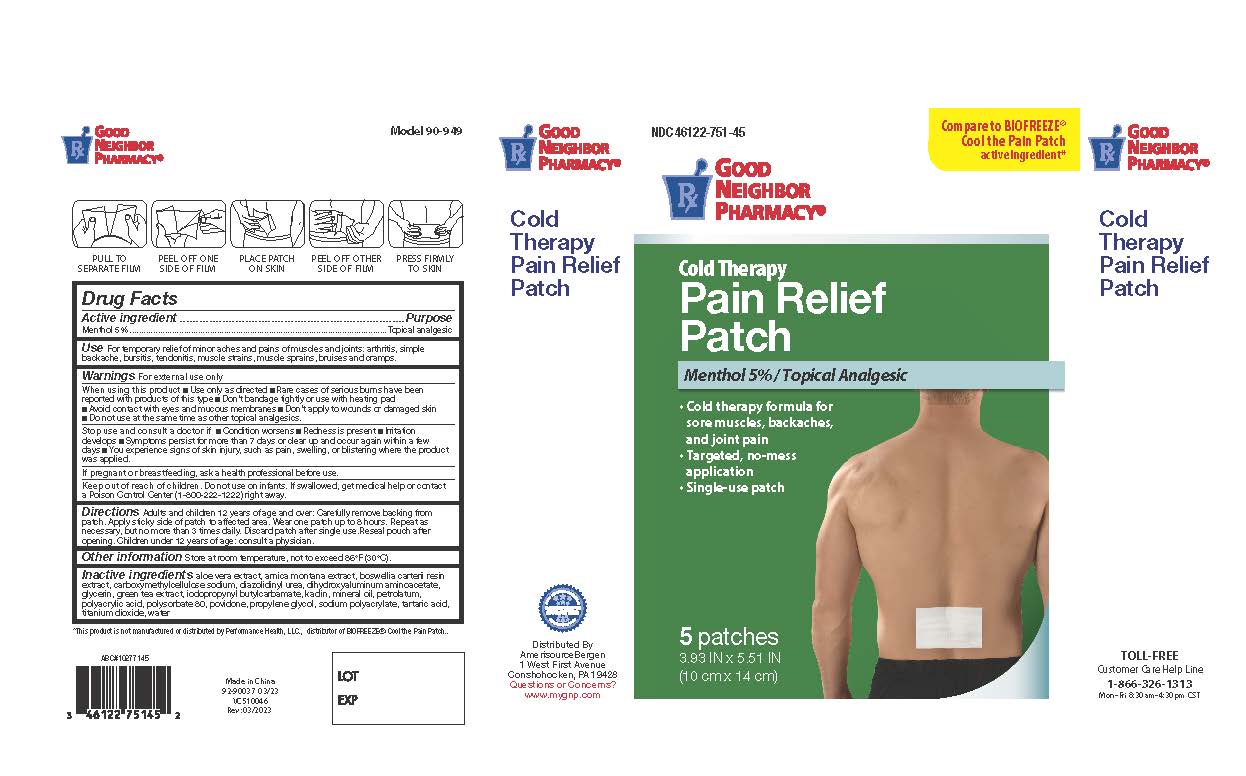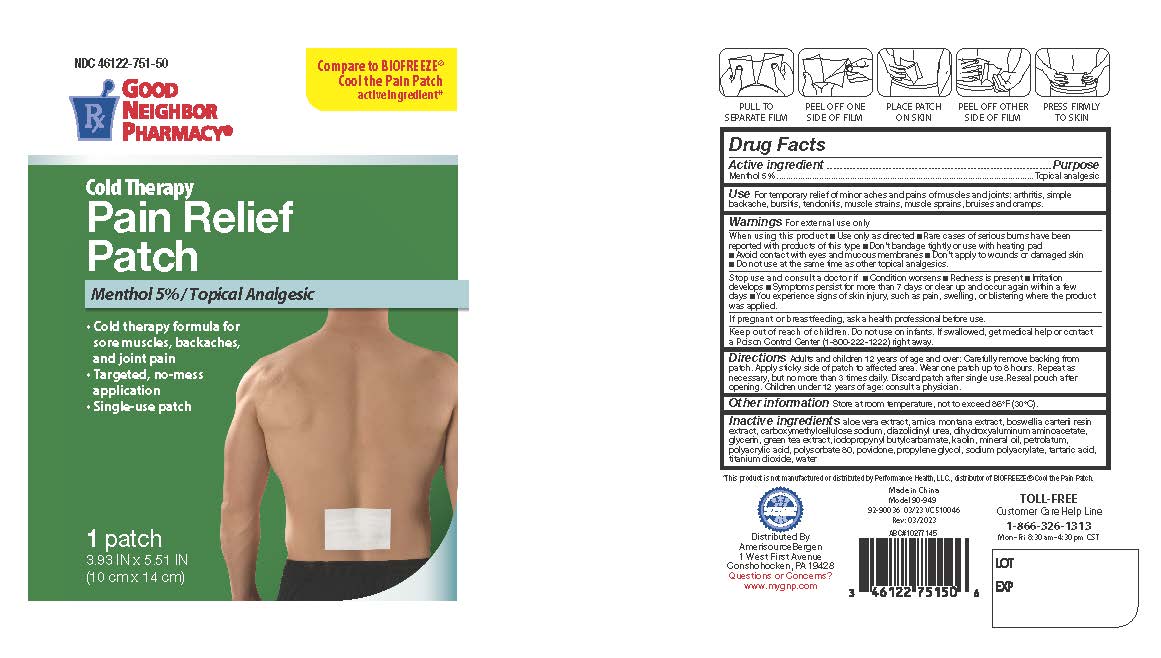 DRUG LABEL: Good Neighbor Pharmacy Cold Therapy Pain Relief Patch
NDC: 46122-751 | Form: PATCH
Manufacturer: Amerisource Bergen
Category: otc | Type: HUMAN OTC DRUG LABEL
Date: 20251222

ACTIVE INGREDIENTS: MENTHOL 5 g/100 g
INACTIVE INGREDIENTS: GREEN TEA LEAF; BOSWELLIA SERRATA RESIN OIL; PROPYLENE GLYCOL; ARNICA MONTANA FLOWER; TARTARIC ACID; POVIDONE; CARBOXYMETHYLCELLULOSE SODIUM, UNSPECIFIED FORM; SODIUM POLYACRYLATE (8000 MW); MINERAL OIL; WATER; POLYACRYLIC ACID (8000 MW); DIAZOLIDINYL UREA; ALOE VERA LEAF; DIHYDROXYALUMINUM AMINOACETATE; GLYCERIN; TITANIUM DIOXIDE; KAOLIN; PETROLATUM; POLYSORBATE 80; IODOPROPYNYL BUTYLCARBAMATE

Good Neighbor Pharmacy Cold Therapy Pain Relief Patch

Active Ingredient

Menthol 5%

Purpose

Topical analgesic

Use

For temporary relief of minor aches and pains of muscles and joints: arthritis, simple backache, bursitis, tendonitis, muscle strains, muscle sprains, bruises and cramps

Warnings

For external use only

When using this product

■Use only as directed ■ Rare cases of serious burns have been reported with products of this type ■Don't bandage tightly or use with heating pad ■ Avoid contact with eyes and mucous membranes ■Don't apply to wounds or damaged skin ■ Do not use at the same time as other topical analgesics.

Stop use and consult a doctor if

o condition worsens

o redness is present

o irritation develops

o symptoms persist for more than 7 days or clear up and occur again within a few days

o you experience signs of skin injury, such as pain, swelling, or blistering where the product was applied

If pregnant or breast-feeding

ask a health professional before use.

Keep out of reach of children and pets

Do not use on infants. If swallowed, get medical help or contact a Poison Control Center (1-800-222-1222) right away.

Directions

Adults and children 12 years of age and over: Carefully remove backing from patch. Apply sticky side of patch to affected area. Wear one patch up to 8 hours. Repeat as necessary, but no more than 3 times daily. Discard patch after single use. Reseal pouch after opening. Children under 12 years of age: consult a physician.

Other information

Store at room temperature, not to exceed 86'F (30'C).

Inactive Ingredient

aloe vera extract, arnica montana extract, boswellia carterii resin extract, carboxymethylcellulose sodium, diazolidinyl urea, dihydroxyaluminum aminoacetate, glycerin, green tea extract, iodopropynyl butylcarbamate, kaolin, mineral oil, petrolatum,
polyacrylic acid, polysorbate 80, povidone, propylene glycol, sodium polyacrylate, tartaric acid, titanium dioxide, water